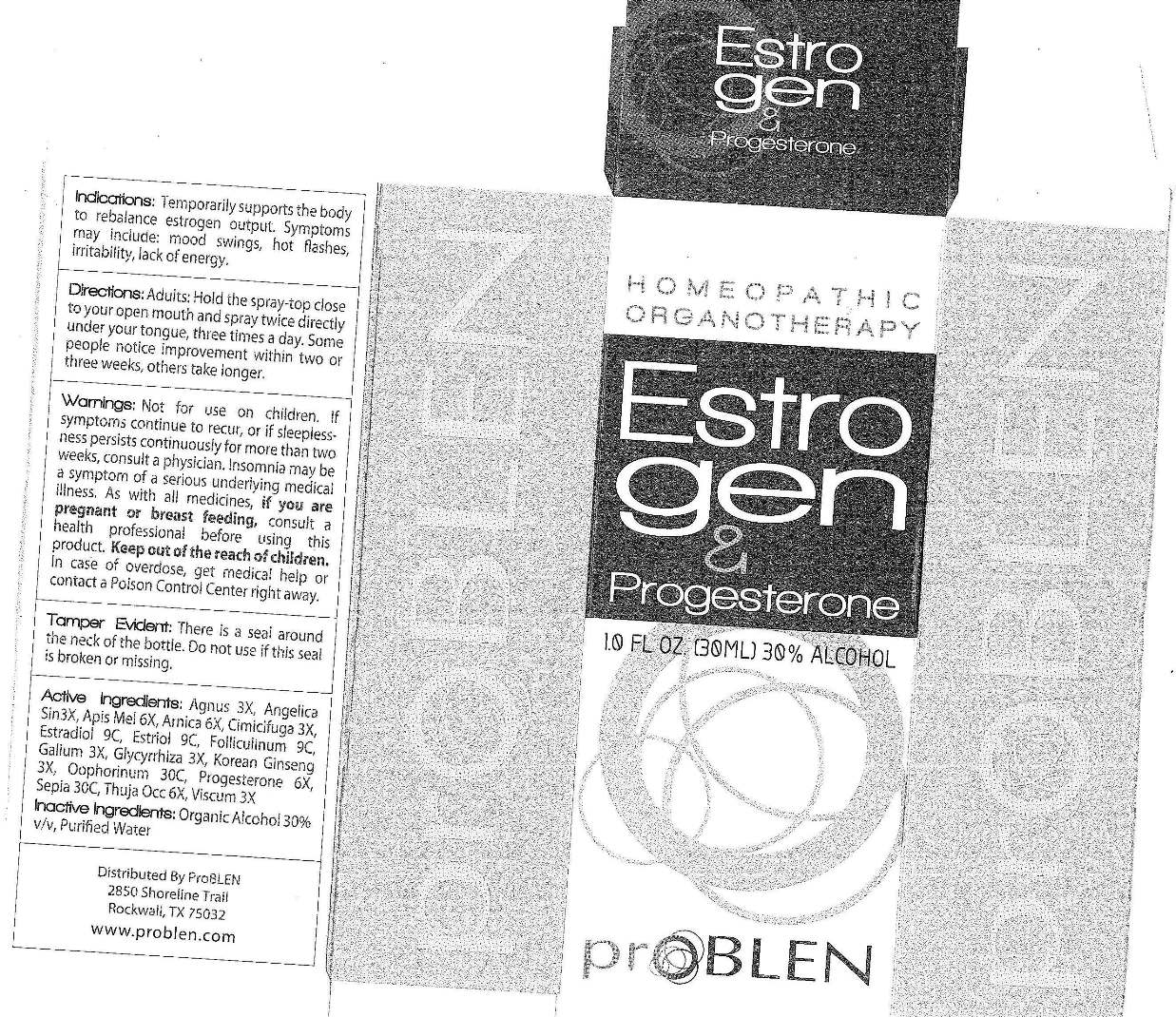 DRUG LABEL: ProBLEN Estrogen and Progesterone
NDC: 50845-0169 | Form: SPRAY
Manufacturer: Liddell Laboratories, Inc.
Category: homeopathic | Type: HUMAN OTC DRUG LABEL
Date: 20120206

ACTIVE INGREDIENTS: CHASTE TREE 3 [hp_X]/1 mL; ANGELICA SINENSIS ROOT 3 [hp_X]/1 mL; APIS MELLIFERA 6 [hp_X]/1 mL; ARNICA MONTANA 6 [hp_X]/1 mL; BLACK COHOSH 3 [hp_X]/1 mL; ESTRADIOL 9 [hp_C]/1 mL; ESTRIOL 9 [hp_C]/1 mL; ESTRONE 9 [hp_C]/1 mL; GALIUM APARINE 3 [hp_X]/1 mL; GLYCYRRHIZA GLABRA 3 [hp_X]/1 mL; ASIAN GINSENG 3 [hp_X]/1 mL; SUS SCROFA OVARY 30 [hp_C]/1 mL; PROGESTERONE 6 [hp_X]/1 mL; SEPIA OFFICINALIS JUICE 30 [hp_C]/1 mL; THUJA OCCIDENTALIS LEAFY TWIG 6 [hp_X]/1 mL; VISCUM ALBUM FRUITING TOP 3 [hp_X]/1 mL
INACTIVE INGREDIENTS: WATER; ALCOHOL

ProBLEN Estrogen and Progesterone

ACTIVE INGREDIENT

ACTIVE INGREDIENTS: Agnus castus 3X, Angelica sinensis, radix 3X, Apis mellifica 6X, Arnica montana 6X, Cimicifuga racemosa 3X, Estradiol 9C, Estriol 9C, Folliculinum 9C, Galium aparine 3X, Glycyrrhiza glabra 3X, Korean ginseng 3X, Oophorinum suis 30C, Progesterone 6X, Sepia 30C, Thuja occidentalis 6X, Viscum album 3X.

PURPOSE

INDICATIONS: Temporarily supports the body to rebalance estrogen output. Symptoms may include: mood swings, hot flashes, irritability, lack of energy.

WARNINGS: Not for use on children.

If symptoms continue to recur, or if sleeplessness persists continuously for more than two weeks, consult a physician. Insomnia may be a symptom of a serious underlying medical illness.

As with all medicines, if you are pregnant or breast feeding, consult a health professional before using this product.

Keep out of reach of children. In case of overdose, get medical help or contact a Poison Control Center right away.

DOSAGE AND ADMINISTRATION

DIRECTIONS: Adults: Hold the spray-top close to your open mouth and spray twice directly under your tongue, three times a day. Some people notice improvement within two or three weeks, others take longer.

INACTIVE INGREDIENT

INACTIVE INGREDIENTS: Organic alcohol 30% v/v, Purified water.

KEEP OUT OF REACH OF CHILDREN. In case of overdose, get medical help or contact a Poison Control Center right away.

INDICATIONS AND USAGE

INDICATIONS: Temporarily supports the body to rebalance estrogen output. Symptoms may include: mood swings, hot flashes, irritability, lack of energy.

QUESTIONS

Distributed by

ProBLEN

2850 Shoreline Trail

Rockwall, TX 75032

www.problen.com

PACKAGE LABEL

HOMEOPATHIC ORGANOTHERAPY

Estrogen and Progesterone

1.O FL OZ (30ML)

proBLEN